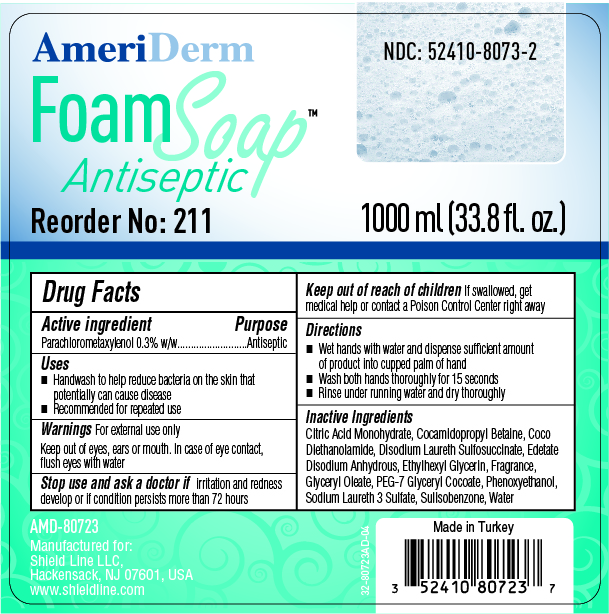 DRUG LABEL: AmeriDerm Antibacterial Wash
NDC: 52410-8073 | Form: LIQUID
Manufacturer: SHIELD LINE LLC
Category: otc | Type: HUMAN OTC DRUG LABEL
Date: 20250815

ACTIVE INGREDIENTS: CHLOROXYLENOL 0.003 mg/1 mL
INACTIVE INGREDIENTS: COCAMIDOPROPYL BETAINE; DISODIUM LAURETH SULFOSUCCINATE; GLYCERYL OLEATE; ETHYLHEXYLGLYCERIN; SULISOBENZONE; WATER; CITRIC ACID MONOHYDRATE; COCO DIETHANOLAMIDE; PEG-7 GLYCERYL COCOATE; ISOPROPYL ALCOHOL; PHENOXYETHANOL; SODIUM LAURETH SULFATE; EDETATE DISODIUM

AMERIDERM Antibacterial Foaming - ALL-211

Drug Facts Active Ingredient

Parachlorometaxylenol 0.3% w/w

Purpose

Antiseptic

Uses

- Handwash to help reduce bacteria on the skin that potentially can cause disease
- Recommended for repeat use

Warnings

- For external use only
- Keep out of eyes, ears or mouth. In case of eye contact, flush eyes with water
- Stop use and ask a doctor if irritation and redness develop or if condition persists for more than 72 hours

Keep out of reach of children

If swallowed, get medical help or contact a Poison Control Center right away

Directions

- Wet hands with water and dispense sufficient amount of product into cupped palm of hand
- Wash both hands thoroughly for 15 seconds
- Rince under running water and dry thoroughly

Inactive Ingredients

Citric Acid Monohydrate, Cocamidopropyl Betaine, Coco Diethanolamide, Disodium Laureth Sulfosuccinate, Edetate Disodium Anhydrous, Ethylhexyl Glycerin, Fragrance, Glyceryl oleate, PEG-7 Glyceryl Cocoate, Phenoxyethanol, Sodium Laureth 3 Sulfate, Sulisobenzone, Water